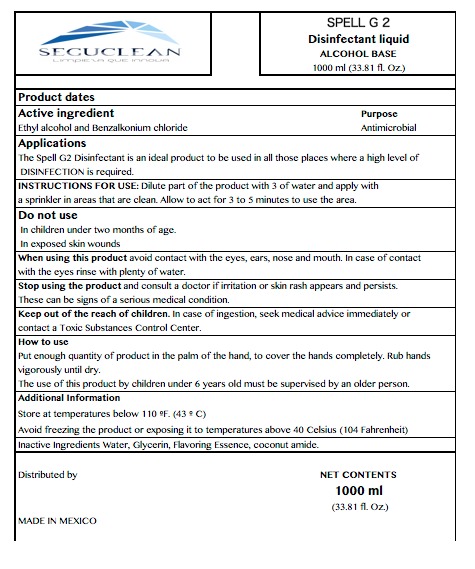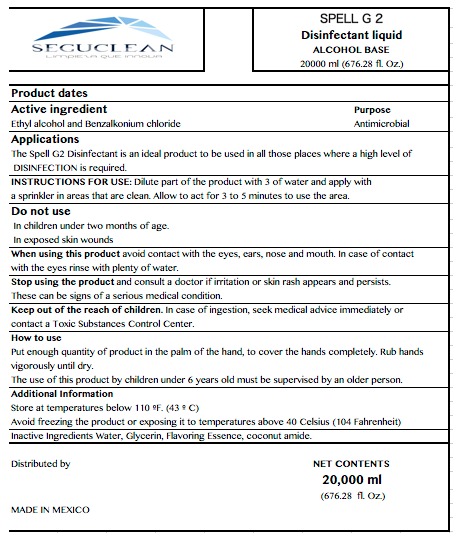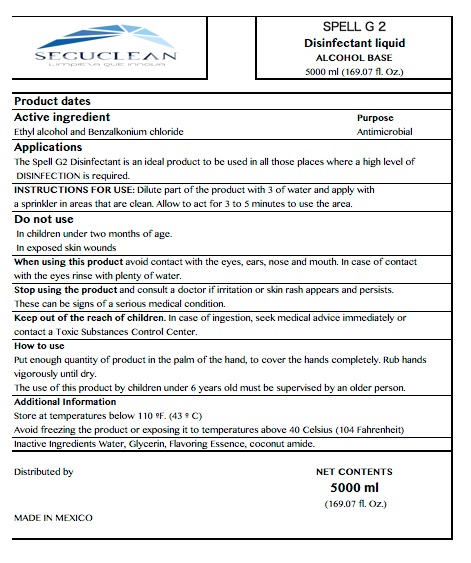 DRUG LABEL: SEGUCLEAN
NDC: 79594-3000 | Form: SOLUTION
Manufacturer: Productos y Servicios de Limpieza Seguclean S.A. de C.V.
Category: otc | Type: HUMAN OTC DRUG LABEL
Date: 20200721

ACTIVE INGREDIENTS: BENZALKONIUM CHLORIDE 0.015 mg/1 mL; ALCOHOL 0.2 mL/1 mL
INACTIVE INGREDIENTS: DIETHANOLAMINE 0.003 mL/1 mL; WATER 0.763 mL/1 mL; GLYCERIN 0.015 mL/1 mL; TRICLOSAN 0.001 mL/1 mL; ROSE OIL 0.003 mL/1 mL

HAND SANITIZER SOLUTION

ACTIVE INGREDIENTS

Active ingredient Ethyl Alcohol, Benzalkonium Chloride

INDICATIONS AND USAGE

Put enough quantity of product in the palm of the heand, to cover completely. Rub hands vigorously until dry.

Dilute part of the product with 3 of water and apply with a sprinkler in areas that are clean. Allow to act for 3 to 5 minutes to use the area.

DOSAGE AND ADMINISTRATION

Put enough quantity of product in the palm of the hand to cover the hands. Rub hands vigorously until dry.

Do not use in children under two months of age.

In exposed skin wounds.

STOP USE

Stop using the product avoid contact with the eyes, ears, nose and mouth. In case of contact with the eyes, rinse with plenty of water.

KEEP OUT OF REACH OF CHILDREN

Keep out of reach of chindren. In case of ingestion, seek medical advice immediately or contact a Toxic Substances Control Center.

WARNINGS AND PRECAUTIONS

Store at temperatures below 110 degrees F (43 C)

WARNINGS

AVOID FREEZING

KEEP OUT OF REACH OF CHILDREN

PURPOSE

PURPOSE ANTIMICROBIAL

INACTIVE INGREDIENTS

WATER, GLYCERIN, ESSENCE, COCONUT AMIDE